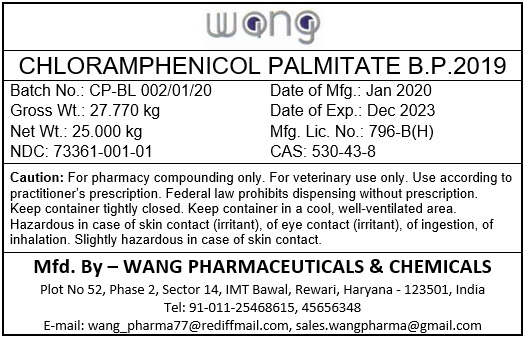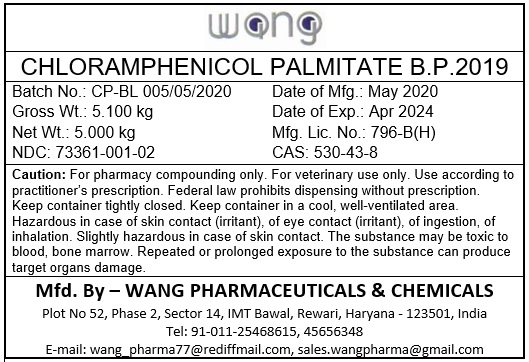 DRUG LABEL: Chloramphenicol Palmitate
NDC: 73361-001 | Form: POWDER
Manufacturer: Wang Pharmaceuticals & Chemicals
Category: other | Type: BULK INGREDIENT
Date: 20200706

ACTIVE INGREDIENTS: CHLORAMPHENICOL PALMITATE 1 kg/1 kg

Chloramphenicol Palmitate